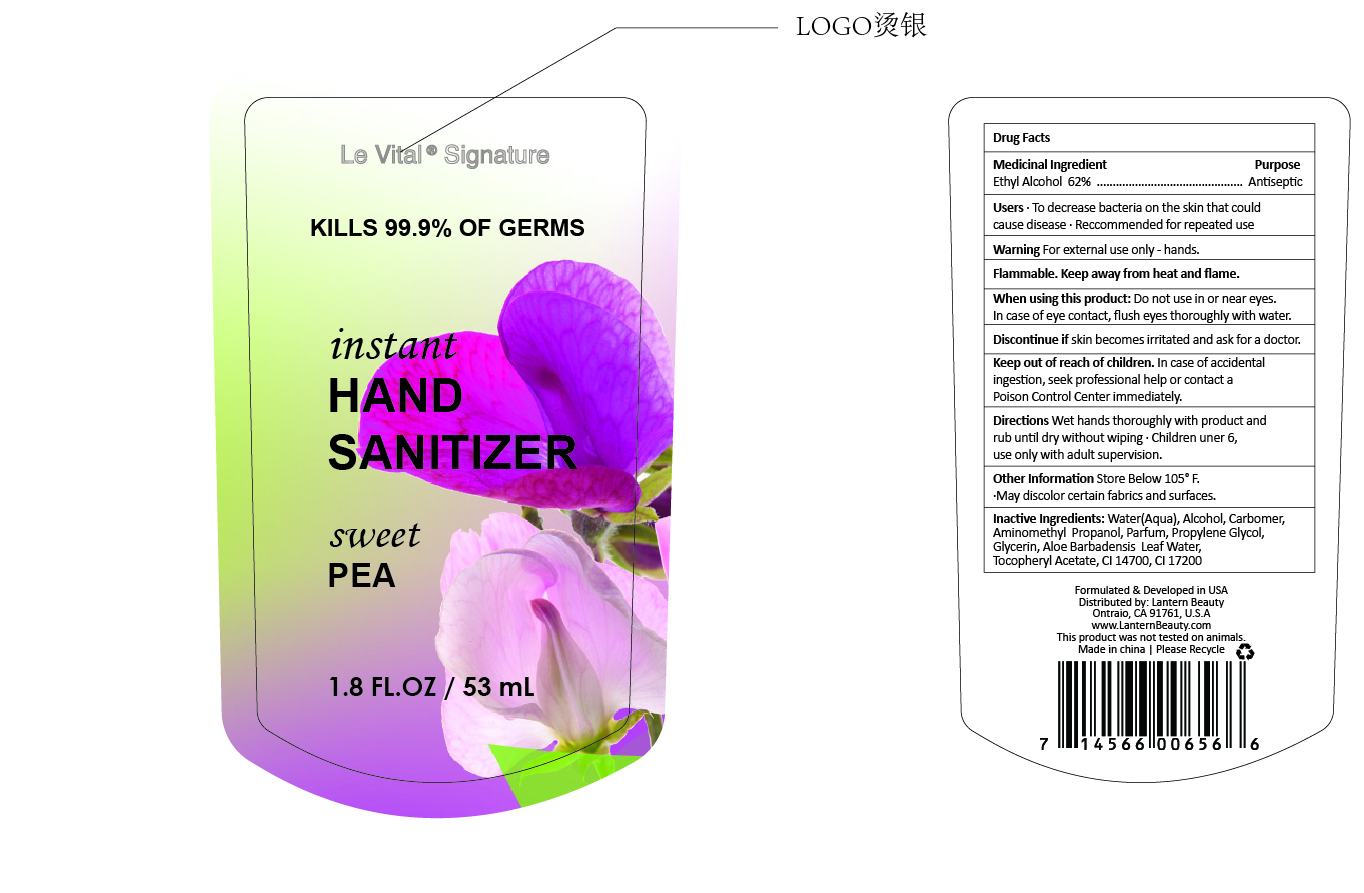 DRUG LABEL: Le Vital hand sanitizer with sweet PEA
NDC: 54860-315 | Form: LIQUID
Manufacturer: Shenzhen Lantern Scicence Co.,Ltd.
Category: otc | Type: HUMAN OTC DRUG LABEL
Date: 20200810

ACTIVE INGREDIENTS: ALCOHOL 62 mL/100 mL
INACTIVE INGREDIENTS: AMINOMETHYLPROPANOL 0.09 mL/100 mL; WATER 37.427659 mL/100 mL; PROPYLENE GLYCOL 0.01 mL/100 mL; CARBOMER 940 0.26 mL/100 mL; GLYCERIN 0.01 mL/100 mL; LATHYRUS ODORATUS SEED 0.2 mL/100 mL; ALOE VERA LEAF 0.001 mL/100 mL; FD&C RED NO. 4 0.0002 mL/100 mL; D&C RED NO. 33 0.00015 mL/100 mL; .ALPHA.-TOCOPHEROL ACETATE 0.001 mL/100 mL

Le Vital hand sanitizer with sweet PEA

Active Ingredient

Active Ingredient Purpose

Ethyl Alcohol 62%（V/V） Antiseptic

Use

Hand sanitizer helps to reduce bacteria that potentially can cause disease.For use when soap and water are not available.

Use(s)

To decrease bacteria on the skin that could cause disease.Recommended for repeated use.

Warning

For external use only-hands

Flammable.Keep away from heat and flame.

WARNINGS AND PRECAUTIONS

For external use only.

Flammable, keep away from heat and flame.

STOP USE

Discontinue if skin becomes irritated and ask a doctor .

Keep out of reach of children. In case of accidental ingestion, seek professional assistance or contact a poson control center immediately.

keep out of reach of children

In case of accidental ingestion,seek professional assistant or contact a Poison Control Center immediately.

DOSAGE AND ADMINISTRATION

Recommended for repeated use.

use anywhere without water.

Inactive ingredients

Water(Aqua),Alcohol,Carbomer, Aminomethyl Propanol,Parfum,Propylene Glycol,Glycerin,Aloe Barbadensis Leaf Water,Tocopheryl Acetate,CI 14700,CI17200.

Directions

Wet hands thoroughly with product and rub until dry without wiping.Children under 6,use only with adult supervision.

When using this product

keep out of eyes. In case of contact with eyes, flush thoroughly with water.

Do not inhale or ingest.

Avoid contact with broken skin.

Other information

Do not store above 105F.

May discolor some fabrics.

Harmful to wood finishes and plastics.

When using this product

Do not use in or near eyes,In case of eye contact ,flush eyes thoroughly with water. Discontinue if skin becomes irritated and ask for a doctor.

Other information

store below 105℉

May discolor some fabrics and surfaces.

Purpose

Antiseptic